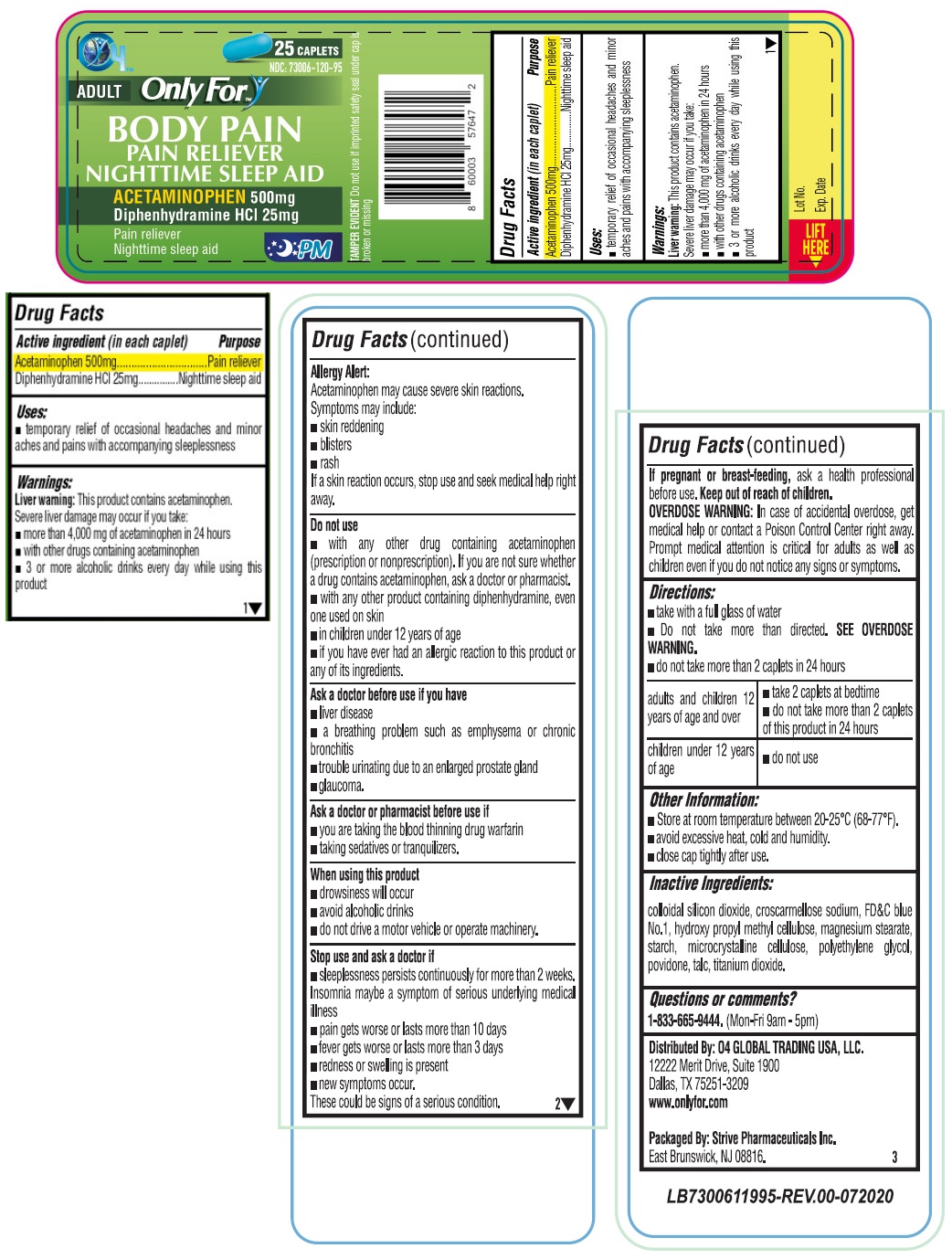 DRUG LABEL: Only For BODY PAIN
NDC: 73006-120 | Form: TABLET
Manufacturer: O4 Global Trading Usa, Llc
Category: otc | Type: HUMAN OTC DRUG LABEL
Date: 20201119

ACTIVE INGREDIENTS: ACETAMINOPHEN 500 mg/1 1; DIPHENHYDRAMINE HYDROCHLORIDE 25 mg/1 1
INACTIVE INGREDIENTS: SILICON DIOXIDE; CROSCARMELLOSE SODIUM; FD&C BLUE NO. 1; HYPROMELLOSE, UNSPECIFIED; MAGNESIUM STEARATE; STARCH, CORN; MICROCRYSTALLINE CELLULOSE; POLYETHYLENE GLYCOL 400; POVIDONE, UNSPECIFIED; TALC; TITANIUM DIOXIDE

Only For™ BODY PAIN

Active ingredient (in each caplet)

Acetaminophen 500mg

Diphenhydramine HCl 25mg

Purpose

Pain reliever

Nighttime sleep aid

Uses:

• temporary relief of occasional headaches and minor aches and pains with accompanying sleeplessness

Warnings:

Liver warning: This product contains acetaminophen. Severe liver damage may occur if you take:

• more than 4,000 mg of acetaminophen in 24 hours

• with other drugs containing acetaminophen

• 3 or more alcoholic drinks every day while using this product

Allergy Alert:

Acetaminophen may cause severe skin reactions.

Symptoms may include:

• skin reddening

• blisters

• rash

If a skin reaction occurs, stop use and seek medical help right away.

Do not use

• with any other drug containing acetaminophen (prescription or nonprescription). If you are not sure whether a drug contains acetaminophen, ask a doctor or pharmacist.

• with any other product containing diphenhydramine, even one used on skin

• in children under 12 years of age

• if you have ever had an allergic reaction to this product or any of its ingredients.

Ask a doctor before use if you have

• liver disease

• a breathing problem such as emphysema or chronic bronchitis

• trouble urinating due to an enlarged prostate gland

• glaucoma.

Ask a doctor or pharmacist before use if

• you are taking the blood thinning drug warfarin

• taking sedatives or tranquilizers.

When using this product

• drowsiness will occur

• avoid alcoholic drinks

• do not drive a motor vehicle or operate machinery.

Stop use and ask a doctor if

• sleeplessness persists continuously for more than 2 weeks. Insomnia may be a symptom of serious underlying medical illness

• pain gets worse or lasts more than 10 days

• fever gets worse or last more than 3 days

• redness or swelling is present

• new symptoms occur.

These could be signs of a serious condition.

If pregnant or breast-feeding, ask a health professional before use.

Keep out of reach of children.

OVERDOSE WARNINGS: In case of accidental overdose, get medical help or contact a Poison Control Center right away. Prompt medical attention is critical for adults as well as for children even if you do not notice any signs or symptoms.

Directions:

• take with a full glass of water

• Do not take more than directed. SEE OVERDOSE WARNING.

• do not take more than 2 caplets in 24 hours

adults and children 12 years of age and over | • take 2 caplets at bedtime; • do not take more than 2 caplets of this product in 24 hours
children under 12 years of age | • do not use

Other Information:

• Store at room temperature between 20-25°C (68-77°F).

• avoid excessive heat, cold and humidity.

• close cap tightly after use.

Inactive Ingredients:

colloidal silicon dioxide, croscarmellose sodium, FD&C blue No.1, hydroxy propyl methyl cellulose, magnesium stearate, starch, microcrystalline cellulose, polyethylene glycol, povidone, talc, titanium dioxide.

Questions or comments?

1-833-665-9444. (Mon-Fri 9am-5pm)

ADULT

PAIN RELIEVER NIGHTTIME SLEEP AID

TAMPER EVIDENT: Do not use if imprinted safety seal under cap is broken or missing

Distributed By: O4 GLOBAL TRADING USA, LLC.

12222 Merit Drive, Suite 1900

Dallas, TX 75251-3209

www.onlyfor.com

Packaged By: Strive Pharmaceuticals Inc.

East Brunswick, NJ 08816.